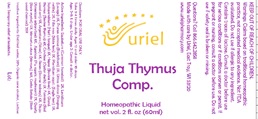 DRUG LABEL: Thuja Thymus comp.
NDC: 48951-9363 | Form: LIQUID
Manufacturer: Uriel Pharmacy Inc.
Category: homeopathic | Type: HUMAN OTC DRUG LABEL
Date: 20210528

ACTIVE INGREDIENTS: FORMICA RUFA 5 [hp_X]/1 mL; PORK KIDNEY 6 [hp_X]/1 mL; LEVISTICUM OFFICINALE ROOT 2 [hp_X]/1 mL; THUJA OCCIDENTALIS WHOLE 6 [hp_X]/1 mL; AMANITA MUSCARIA FRUITING BODY 7 [hp_X]/1 mL; EQUISETUM ARVENSE TOP 2 [hp_X]/1 mL; ACTIVATED CHARCOAL 20 [hp_X]/1 mL; SLOE 2 [hp_X]/1 mL; URTICA DIOICA 2 [hp_X]/1 mL; ASPLENIUM SCOLOPENDRIUM TOP 3 [hp_X]/1 mL; SILVER 6 [hp_X]/1 mL; MERCURY 14 [hp_X]/1 mL; DRYOPTERIS FILIX-MAS ROOT 3 [hp_X]/1 mL; PTERIDIUM AQUILINUM WHOLE 3 [hp_X]/1 mL; SILICON DIOXIDE 12 [hp_X]/1 mL; BEEF LIVER 4 [hp_X]/1 mL; BOS TAURUS THYMUS 4 [hp_X]/1 mL; OSTREA EDULIS SHELL 5 [hp_X]/1 mL
INACTIVE INGREDIENTS: ALCOHOL; LACTOSE, UNSPECIFIED FORM; WATER

Thuja Thymus comp.

INDICATIONS AND USAGE

Directions: FOR ORAL USE ONLY.

DOSAGE AND ADMINISTRATION

Take 3-4 times daily. Ages 12 and older: 10 drops. Ages 2-11: 5 drops. Under age 2: Consult a doctor.

ACTIVE INGREDIENT

Active Ingredients: Equisetum (Common horsetail) 2X, Levisticum (Lovage) 2X, Prunus spinosa (Blackthorn) 2X, Urtica dioica (Stinging nettle) 2X, Filix mas (Male fern) 3X, Pteridium aquil. (Eagle fern) 3X, Scolopendrium (Hart’s tongue) 3X, Hepar (Bovine liver) 4X, Gland. thymus (Bovine thymus) 4X, Conchae (Oyster shells) 5X, Formica (Red wood ant) 5X, Argentum (Silver) 6X, Renes (Bovine kidneys) 6X, Thuja (American arborvitae) 6X, Agaricus (Fly agaric mushroom) 7X, Quartz (Rock crystal) 12X, Mercurius vivus (Mercury) 14X, Carbo Betula (Birch wood charcoal) 20X

INACTIVE INGREDIENT

Inactive Ingredients: Distilled water, 20% Organic cane alcohol, Lactose

PURPOSE

Use: Temporary relief of headache.

KEEP OUT OF REACH OF CHILDREN.

WARNINGS

Warnings: Claims based on traditional homeopathic practice, not accepted medical evidence. Not FDA evaluated. Do not use if allergic to any ingredient. Contains traces of lactose. Consult a doctor before use for serious conditions or if conditions worsen or persist. If pregnant or nursing, consult a doctor before use. Do not use if safety seal is broken or missing.

Questions? Call 866.642.2858
Made with care by Uriel, East Troy, WI 53120
www.urielpharmacy.com Lot: